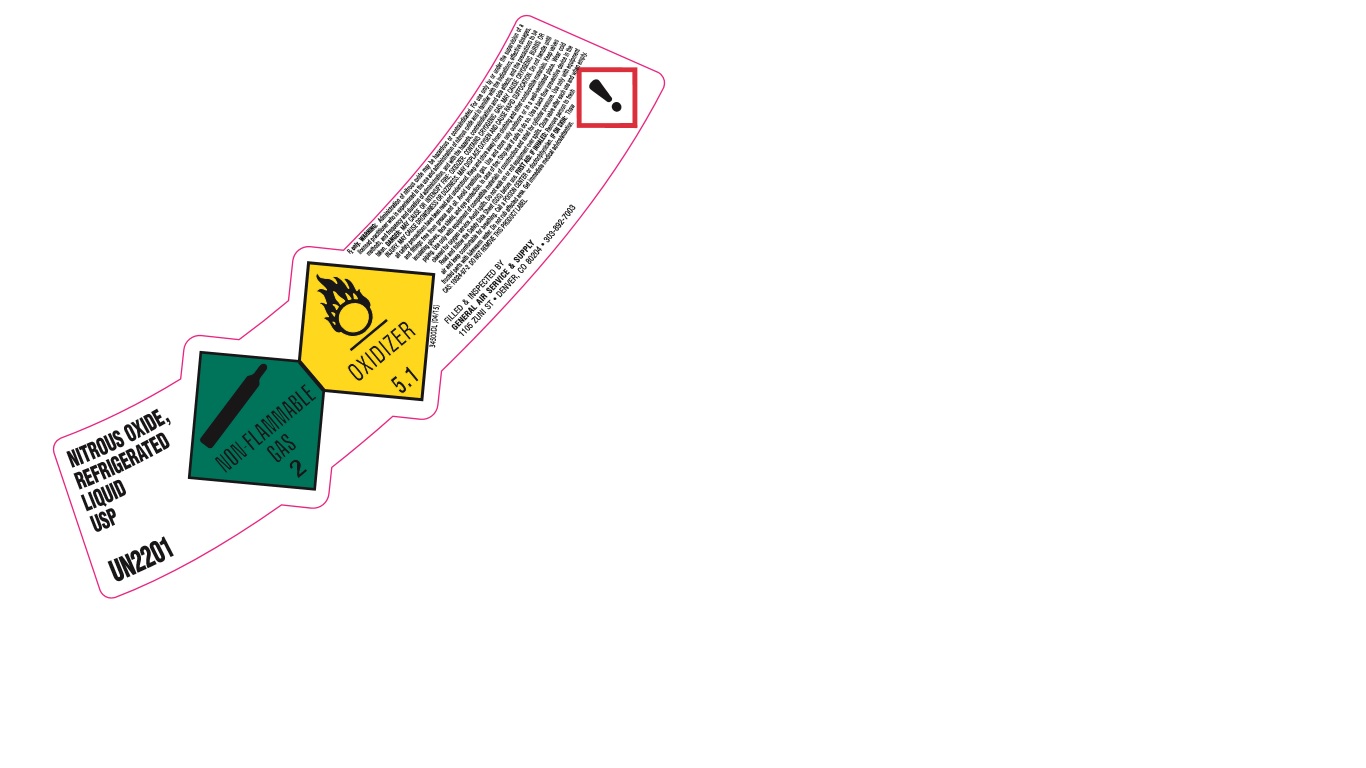 DRUG LABEL: Nitrous Oxide
NDC: 21220-122 | Form: GAS
Manufacturer: General Air Service & Supply Co
Category: prescription | Type: HUMAN PRESCRIPTION DRUG LABEL
Date: 20251126

ACTIVE INGREDIENTS: NITROUS OXIDE 995 mL/1 L

Nitrous Oxide

PACKAGE LABEL

NITROUS OXIDE,
REFRIGERATED LIQUID USP UN1070
NON-FLAMMABLE GAS 2 OXIDIZER 5.1
34500DL (04/15)
Rx only. WARNING: Administration of Nitrous Oxide may be hazardous or contraindicated. For use only by or under the supervision of a licensed practitioner who is experienced in the use and administration of nitrous oxide and is familiar with the indications, effective dosages, methods, and frequency and duration of administration, and with the hazards, contraindications and side effects, and the precautions to be taken. DANGER: MAY CAUSE OR INTENSIFY FIRE; OXIDIZER. CONTAINS CRYOGENIC GAS; MAY CAUSE CRYOGENIC BURNS OR INJURY. MAY CAUSE DROWSINESS OR DIZZINESS. MAY DISPLACE OXYGEN AND CAUSE RAPID SUFFOCATION. Do not handle until all safety precautions have been read and understood. Keep and store away from clothing and other combustible materials. Keep valves and fittings free from grease and oil. Avoid breathing gas. Use and store only outdoors or in a well-ventilated place. Wear cold insulating gloves, face shield, and eye protection. In case of fire: stop leak if safe to do so. Use a back flow preventive device in the piping. Use only with equipment of compatible materials of construction and rated for cylinder pressure. Use only with equipment cleaned for oxygen service. Avoid spills. Do not walk on or roll equipment over spills. Close value after each use and when empty. Read and follow the Safety Data Sheet (SDS) before use. FIRST AID: IF INHALED: Remove person to fresh air and keep comfortable for breathing. Call a POISON CENTER or doctor/physician. IF ON SKIN: Thaw frosted parts with lukewarm water. Do not rub affected area. Get immediate medical advice/attention. CAS: 10024-97-2 DO NOT REMOVE THIS PRODUCT LABEL
FILLED and INSPECTED BY
GENERAL AIR SERVICE and SUPPLY
1105 ZUNI ST. DENVER, CO 80204. 303-892-7003